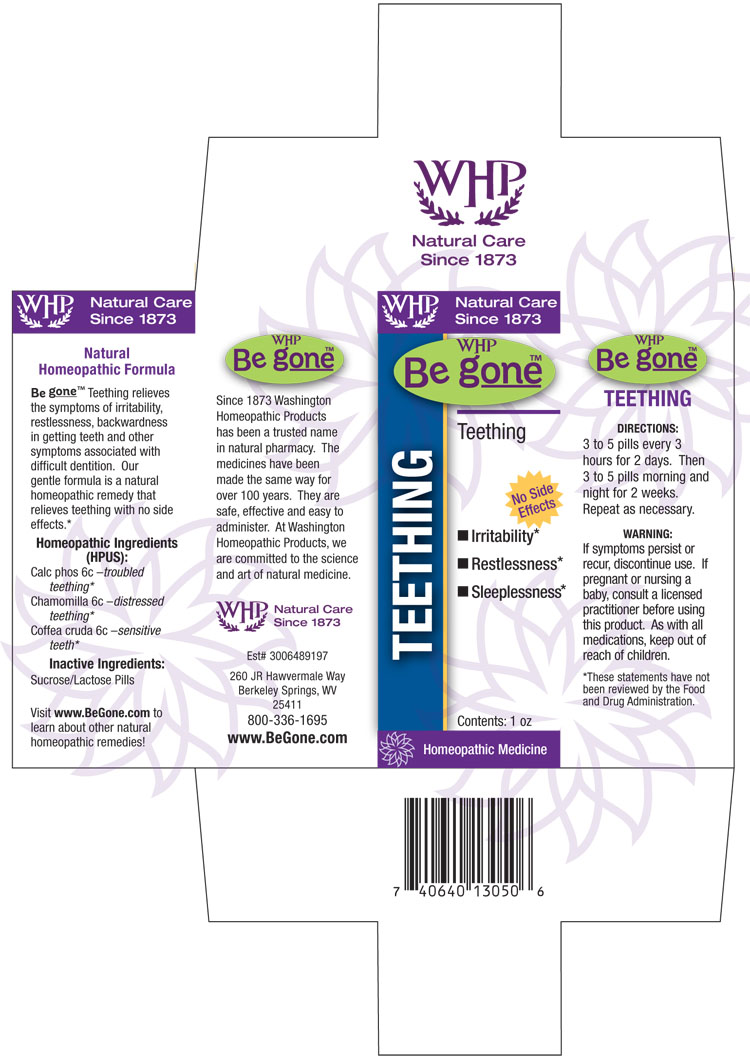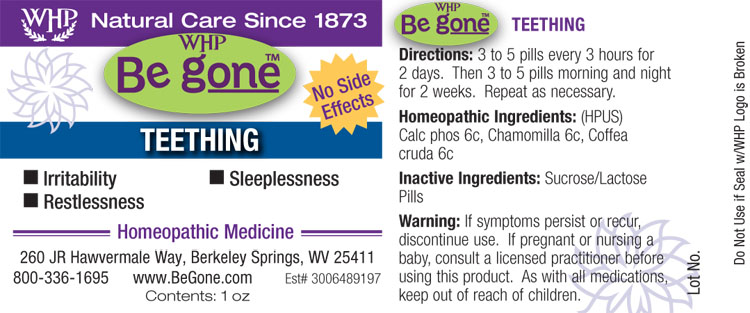 DRUG LABEL: WHP Be gone Teething
NDC: 68428-862 | Form: PELLET
Manufacturer: Washington Homeopathic Products
Category: homeopathic | Type: HUMAN OTC DRUG LABEL
Date: 20140508

ACTIVE INGREDIENTS: TRIBASIC CALCIUM PHOSPHATE 6 [hp_C]/1 1; MATRICARIA CHAMOMILLA 6 [hp_C]/1 1; ARABICA COFFEE BEAN 6 [hp_C]/1 1
INACTIVE INGREDIENTS: SUCROSE; LACTOSE

DRUG FACTS

ACTIVE INGREDIENTS

CALC PHOS

CHAMOMILLA

COFFEA CRUDA

USES

To relieve the symptoms of irritability restlessness, backwardness in getting teeth and other symptoms associated with difficult dentition.

KEEP OUT OF REACH OF CHILDREN

AS with all medications, keep out of reach of children.

INDICATIONS

Calc phos 6c –troubled teething*

Chamomilla 6c –distressed teething*

Coffea cruda 6c –sensitive teething*

■ Irritability ■ Restlessness ■ Sleeplessness

*These statements have not been reviewed by the Food and Drug Administration.

STOP USE AND ASK DOCTOR

If symptoms persist or recur, discontinue use. If pregnant or nursing a baby, consult a licensed practitioner before using this product.

DIRECTIONS

3 to 5 pills every 3 hours for 2 days. Then 3 to 5 pills morning and night for 2 weeks. Repeat as necessary.

INACTIVE INGREDIENTS

Sucrose/Lactose Pills